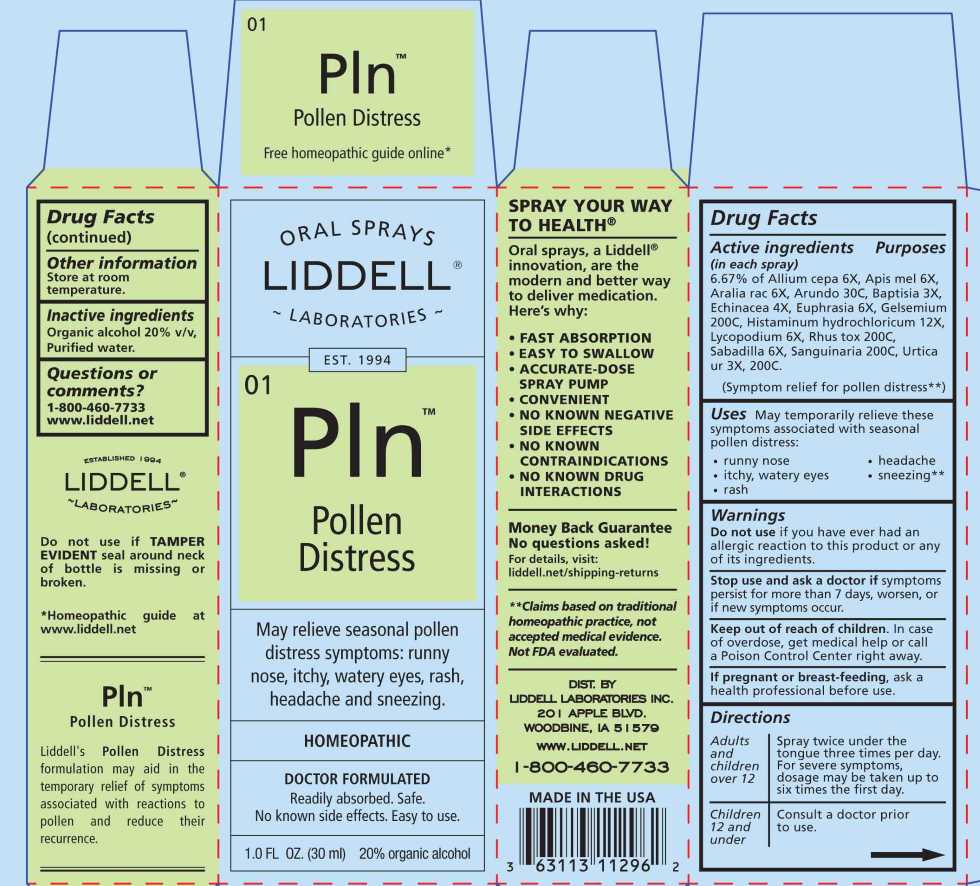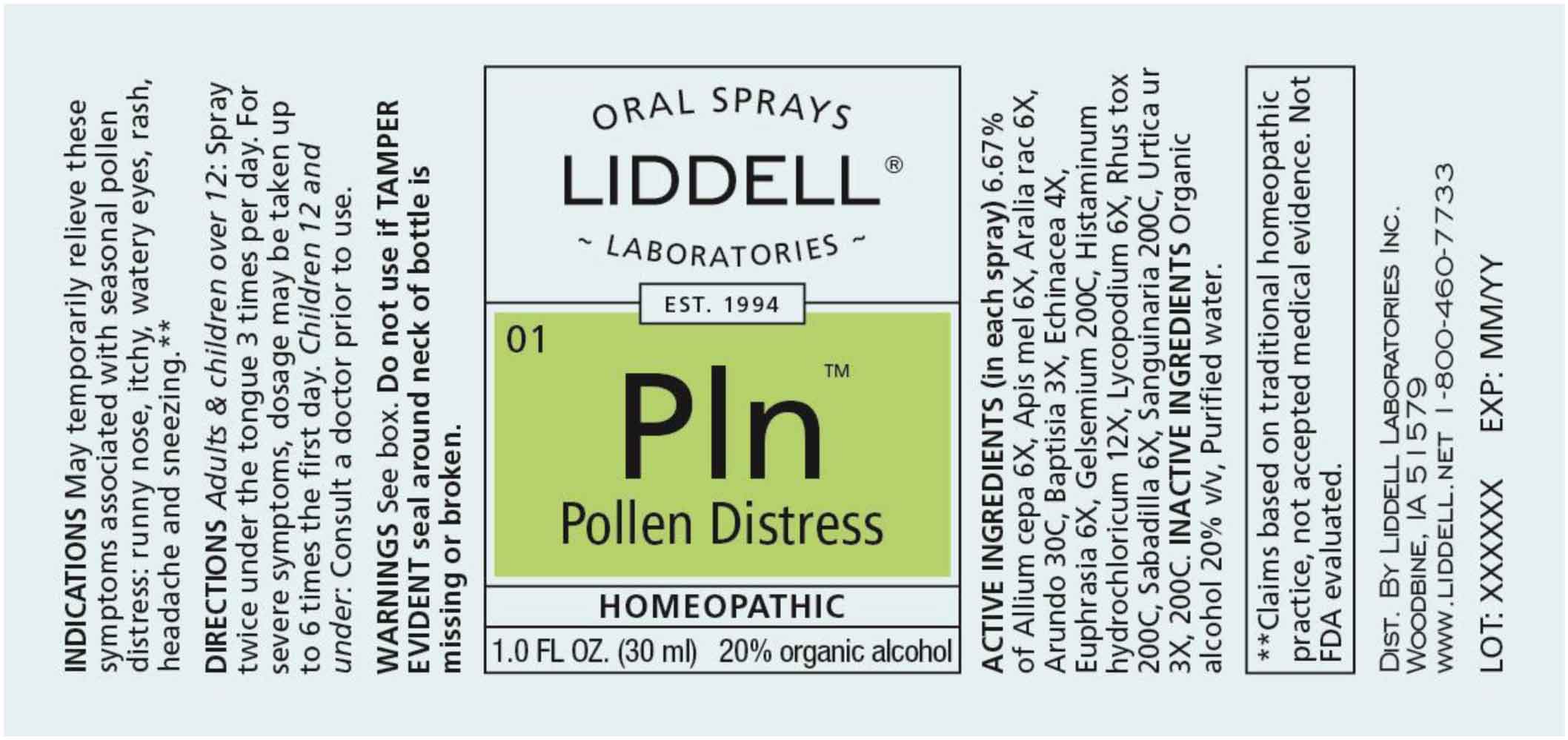 DRUG LABEL: Pollen Distress
NDC: 50845-0284 | Form: SPRAY
Manufacturer: Liddell Laboratories, Inc.
Category: homeopathic | Type: HUMAN OTC DRUG LABEL
Date: 20260126

ACTIVE INGREDIENTS: ONION 6 [hp_X]/1 mL; APIS MELLIFERA 6 [hp_X]/1 mL; ARALIA RACEMOSA ROOT 6 [hp_X]/1 mL; ARUNDO PLINIANA ROOT 30 [hp_C]/1 mL; BAPTISIA TINCTORIA ROOT 3 [hp_X]/1 mL; ECHINACEA ANGUSTIFOLIA WHOLE 4 [hp_X]/1 mL; EUPHRASIA STRICTA 6 [hp_X]/1 mL; GELSEMIUM SEMPERVIRENS ROOT 200 [hp_C]/1 mL; HISTAMINE DIHYDROCHLORIDE 12 [hp_X]/1 mL; LYCOPODIUM CLAVATUM SPORE 6 [hp_X]/1 mL; TOXICODENDRON PUBESCENS LEAF 200 [hp_X]/1 mL; SCHOENOCAULON OFFICINALE SEED 6 [hp_C]/1 mL; SANGUINARIA CANADENSIS ROOT 200 [hp_C]/1 mL; URTICA URENS WHOLE 3 [hp_X]/1 mL
INACTIVE INGREDIENTS: WATER; ALCOHOL

DRUG FACTS:

ACTIVE INGREDIENTS:

(in each spray) 6.67% of Allium Cepa 6X, Apis Mellifica 6X, Aralia Racemosa 6X, Arundo Mauritanica 30C, Baptisia Tinctoria 3X, Echinacea 4X, Euphrasia Officinalis 6X, Gelsemium Sempervirens 200C, Histaminum Hydrochloricum 12X, Lycopodium Clavatum 6X, Rhus Tox 200C, Sabadilla 6X, Sanguinaria Canadensis 200C, Urtica Urens 3X, 200C.

PURPOSE

May temporarily relieve these symptoms associated with seasonal pollen distress:

• runny nose

• itchy, watery eyes

• rash

• headache

• sneezing**

**Claims based on traditional homeopathic practice, not accepted medical evidence. Not FDA evaluated.

WARNINGS:

Do not use if you have ever had an allergic reaction to this product or any of its ingredients.

Stop use and ask a doctor if symptoms persist for more than 7 days, worsen, or if new symptoms occur.

Keep out of reach of children. In case of overdose, get medical help or call a Poison Control Center right away.

If pregnant or breast feeding, ask a health professional before use.

Do not use if TAMPER EVIDENT seal around neck of bottle is missing or broken.

Store at room temperature.

KEEP OUT OF REACH OF CHILDREN:

In case of overdose, get medical help or call a Poison Control Center right away.

DIRECTIONS:

Adults and children over 12: Spray twice under the tongue three times per day. For severe symptoms, dosage may be taken up to six times the first day.

Children 12 and under: Consult a doctor prior to use.

INDICATIONS:

May temporarily relieve these symptoms associated with seasonal pollen distress:

• runny nose

• itchy, watery eyes

• rash

• headache

• sneezing**

**Claims based on traditional homeopathic practice, not accepted medical evidence. Not FDA evaluated.

INACTIVE INGREDIENTS:

Organic alcohol 20% v/v, Purified water.

QUESTIONS:

DIST. BY

LIDDELL LABORATORIES INC.

201 APPLE BLVD.

WOODBINE, IA 51579

WWW.LIDDELL.NET

1-800-460-7733

PACKAGE LABEL DISPLAY:

ORAL SPRAYS

LIDDELL
LABORATORIES

EST. 1994

01 Pln
Pollen Distress

HOMEOPATHIC

DOCTOR FORMULATED

Readily absorbed. Safe.
No Known side effects. Easy to use.

1.0 FL OZ (30 ml)